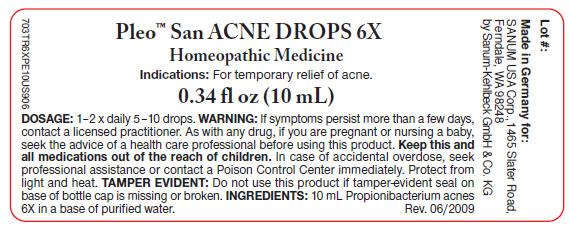 DRUG LABEL: Pleo San Acne
NDC: 60681-3601 | Form: SOLUTION/ DROPS
Manufacturer: Sanum Kehlbeck GmbH & Co. KG
Category: homeopathic | Type: HUMAN OTC DRUG LABEL
Date: 20110801

ACTIVE INGREDIENTS: propionibacterium acnes 6 [hp_X]/10 mL
INACTIVE INGREDIENTS: water

Pleo™ San
ACNE
DROPS 6X

Homeopathic Medicine

0.34 fl oz
(10 mL)

Indications

PURPOSE

For temporary relief of acne.

INGREDIENTS

INACTIVE INGREDIENT

10 mL Propionibacterium acnes 6X in a base of purified water.

Tamper Evident

Do not use this product if tamper-evident seal on base of bottle cap is missing or broken or if imprinted security strip on carton is torn.

DOSAGE

1-2 × daily 5-10 drops.

WARNING

If symptoms persist more than a few days, contact a licensed practitioner. As with any drug, if you are pregnant or nursing a baby, seek the advice of a health care professional before using this product.

KEEP OUT OF REACH OF CHILDREN

Keep this and all medications out of the reach of children. In case of accidental overdose, seek professional assistance or contact a Poison Control Center immediately.

STORAGE AND HANDLING

Protect from light and heat.

Made in Germany

Distributed by:
SANUM USA Corp.
1465 Slater Road
Ferndale, WA 98248

Manufactured By:
Sanum-Kehlbeck,
GmbH & Co. KG

Rev. 12/2007

PRINCIPAL DISPLAY PANEL - 10 mL Label

Pleo™ San ACNE DROPS 6X

Homeopathic Medicine

Indications: For temporary relief of acne.

0.34 fl oz (10 mL)

DOSAGE: 1–2 × daily 5–10 drops. WARNING: If symptoms persist more than a few days,
contact a licensed practitioner. As with any drug, if you are pregnant or nursing a baby,
seek the advice of a health care professional before using this product. Keep this and
all medications out of reach of children. In case of accidental overdose, seek
professional assistance or contact a Poison Control Center immediately. Protect from
light and heat. TAMPER EVIDENT: Do not use this product if tamper-evident seal on
base of bottle cap is missing or broken. INGREDIENTS: 10 mL Propionibacterium acnes
6X in a base of purified water.
Rev. 06/2009